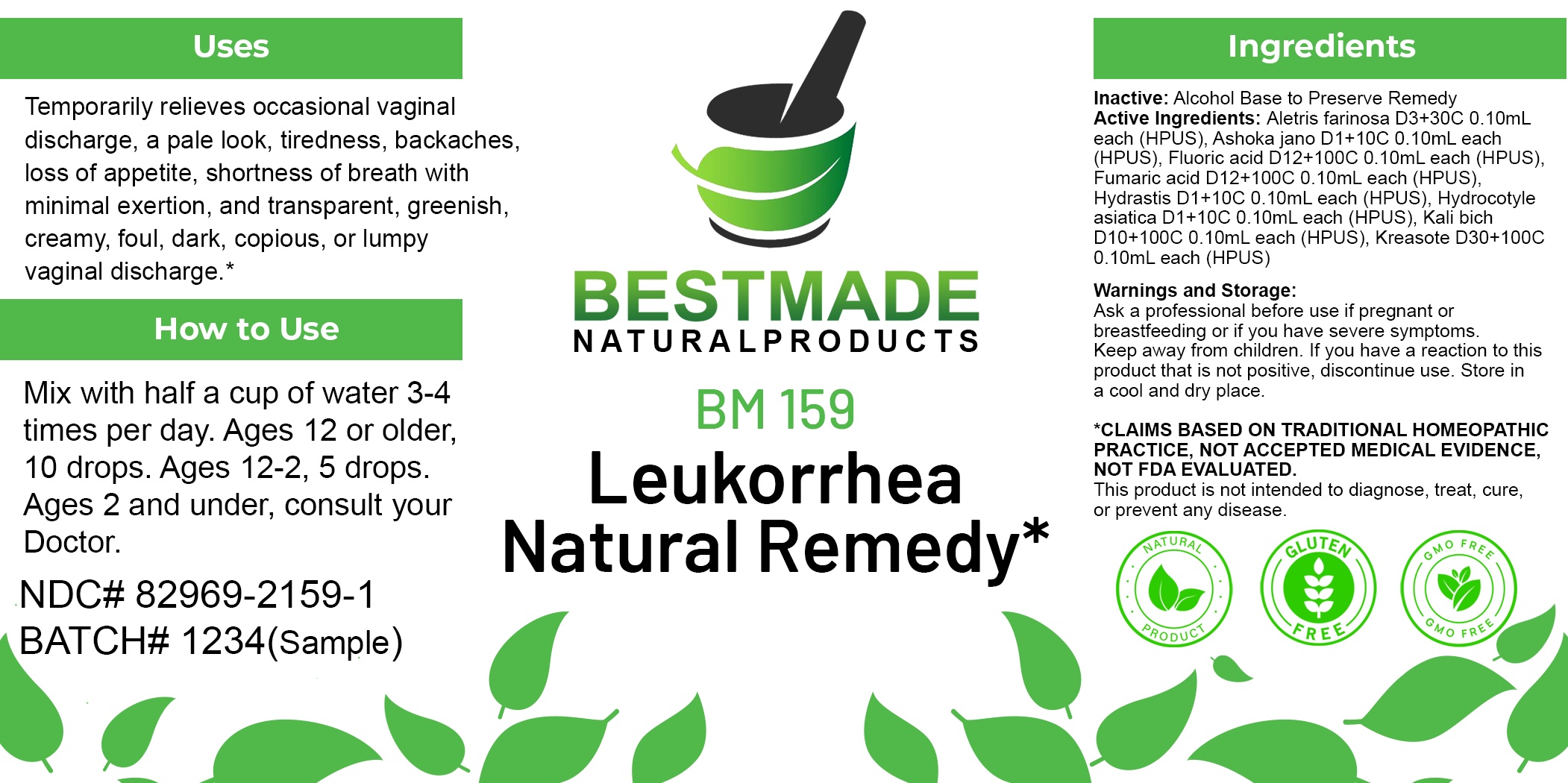 DRUG LABEL: Bestmade Natural Products BM159
NDC: 82969-2159 | Form: LIQUID
Manufacturer: Bestmade Natural Products
Category: homeopathic | Type: HUMAN OTC DRUG LABEL
Date: 20250218

ACTIVE INGREDIENTS: CENTELLA ASIATICA WHOLE 30 [hp_C]/30 [hp_C]; HYDROFLUORIC ACID 30 [hp_C]/30 [hp_C]; ALETRIS FARINOSA ROOT 30 [hp_C]/30 [hp_C]; POTASSIUM DICHROMATE 30 [hp_C]/30 [hp_C]; FUMARIC ACID 30 [hp_C]/30 [hp_C]; GOLDENSEAL 30 [hp_C]/30 [hp_C]; SARACA INDICA BARK 30 [hp_C]/30 [hp_C]; WOOD CREOSOTE 30 [hp_C]/30 [hp_C]
INACTIVE INGREDIENTS: ALCOHOL 30 [hp_C]/30 [hp_C]

BM159

ACTIVE INGREDIENT

ACTIVE INGREDIENTS: Aletris farinosa D3+30C 0.10mL each (HPUS), Ashoka jano D1+10C 0.10mL each (HPUS), Fluoric acid D12+100C 0.10mL each (HPUS), Fumaric acid D12+100C 0.10mL each (HPUS), Hydrastis D1+10C 0.10mL each (HPUS), Hydrocotyle asiatica D1+10C 0.10mL each (HPUS), Kali bich D10+100C 0.10mL each (HPUS), Kreasote D30+100C 0.10mL each (HPUS)

DOSAGE AND ADMINISTRATION

How to Use

Mix with half a cup of water 3-4 times per day. Ages 12 or older, 10 drops. Ages 12-2, 5 drops. Ages 2 and under, consult your Doctor.

Inactive:

Alcohol Base to Preserve Product

Uses
Temporarily relieves occasional vaginal, discharge, a pale look, tiredness, backaches, loss of appetite, shortness of breath with minimal exertion, and transparent, greenish creamy, foul, dark, copious, or lumpy vaginal discharge.*

Uses
Temporarily relieves occasional vaginal, discharge, a pale look, tiredness, backaches, loss of appetite, shortness of breath with minimal exertion, and transparent, greenish creamy, foul, dark, copious, or lumpy vaginal discharge.*

KEEP OUT OF REACH OF CHILDREN

Warnings and Storage:

Ask a professional before use if pregnant or breastfeeding or if you have severe symptoms.

Keep away from children. If you have a reaction to this product that is not positive, discontinue use. Store in a cool and dry place

*CLAIMS BASED ON TRADITIONAL HOMEOPATHIC PRACTICE, NOT ACCEPTED MEDICAL EVIDENCE NOT FDA EVALUATED.
This product is not intended to diagnose, treat, cure, or prevent any disease.

Warnings and Storage:

Ask a professional before use if pregnant or breastfeeding or if you have severe symptoms.

Keep away from children. If you have a reaction to this product that is not positive, discontinue use. Store in a cool and dry place

*CLAIMS BASED ON TRADITIONAL HOMEOPATHIC PRACTICE, NOT ACCEPTED MEDICAL EVIDENCE NOT FDA EVALUATED.
This product is not intended to diagnose, treat, cure, or prevent any disease.

Entire package label